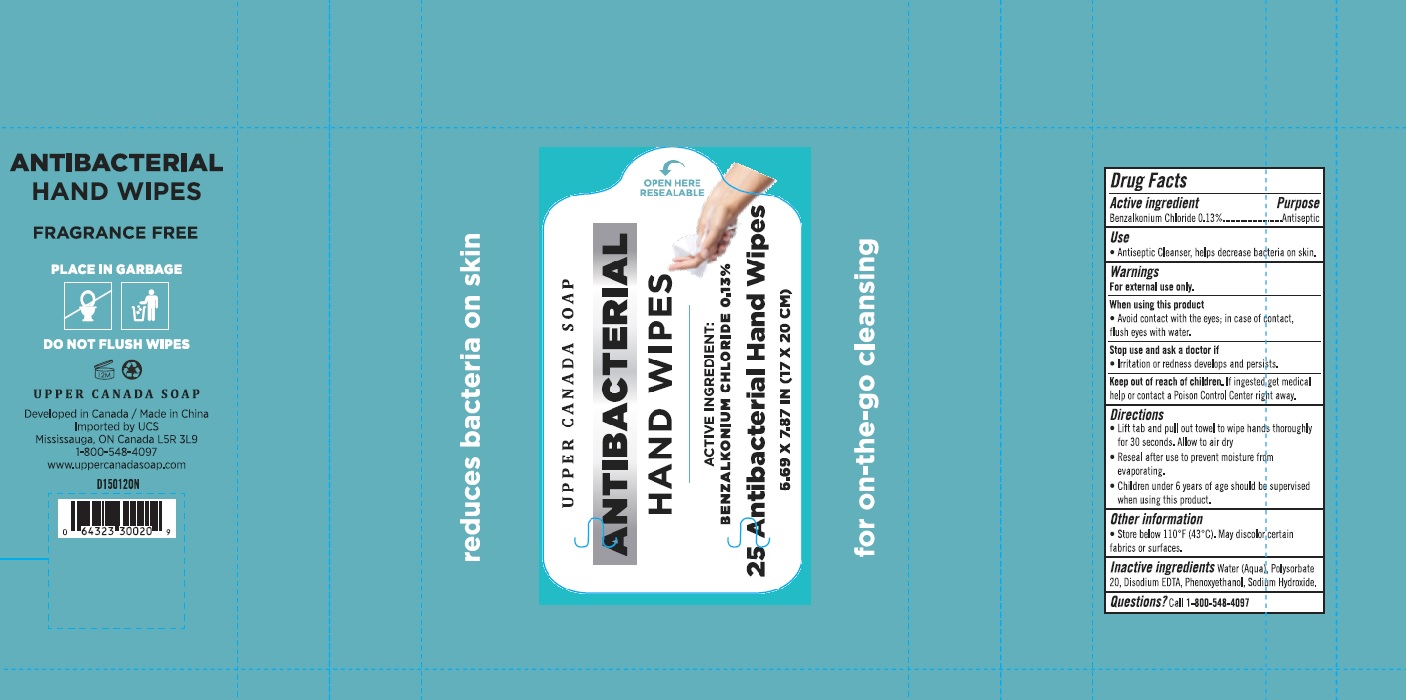 DRUG LABEL: Antibacterial Hand Wipes
NDC: 78936-018 | Form: CLOTH
Manufacturer: Hangzhou Caring Cleaning Commodity Co., LTD
Category: otc | Type: HUMAN OTC DRUG LABEL
Date: 20201006

ACTIVE INGREDIENTS: BENZALKONIUM CHLORIDE 0.13 1/1 1
INACTIVE INGREDIENTS: WATER; POLYSORBATE 20; EDETATE DISODIUM ANHYDROUS; PHENOXYETHANOL; SODIUM HYDROXIDE

Drug Facts

Active ingredient

Benzalkonium Chloride 0.13%

Purpose

Antiseptic

Use

Antiseptic cleanser, helps decrease bacteria on skin.

Warnings

For external use only

When using this product

Avoid contact with the eyes; in case of contact, flus eyes with water.

Keep out of reach of children.

If ingested, get medical help or contact a Poison Control Center right away.

Directions

- Lift tab and pull out twoel to wipe hands thoroughly for 30 seconds. Allow to air dry.
- Reseal after use to prevent moisture from evaporating.
- Children under 6 years of age should be supervised when using this product.

Other information

Store below 110°F (43°C). May discolor certain fabrics or surfaces.

Inactive ingredients

Water (Aqua), Polysorbate 20, Disodium EDTA, Phenoxyethanol, Sodium Hydroxide.

Questions?

1-800-548-4097